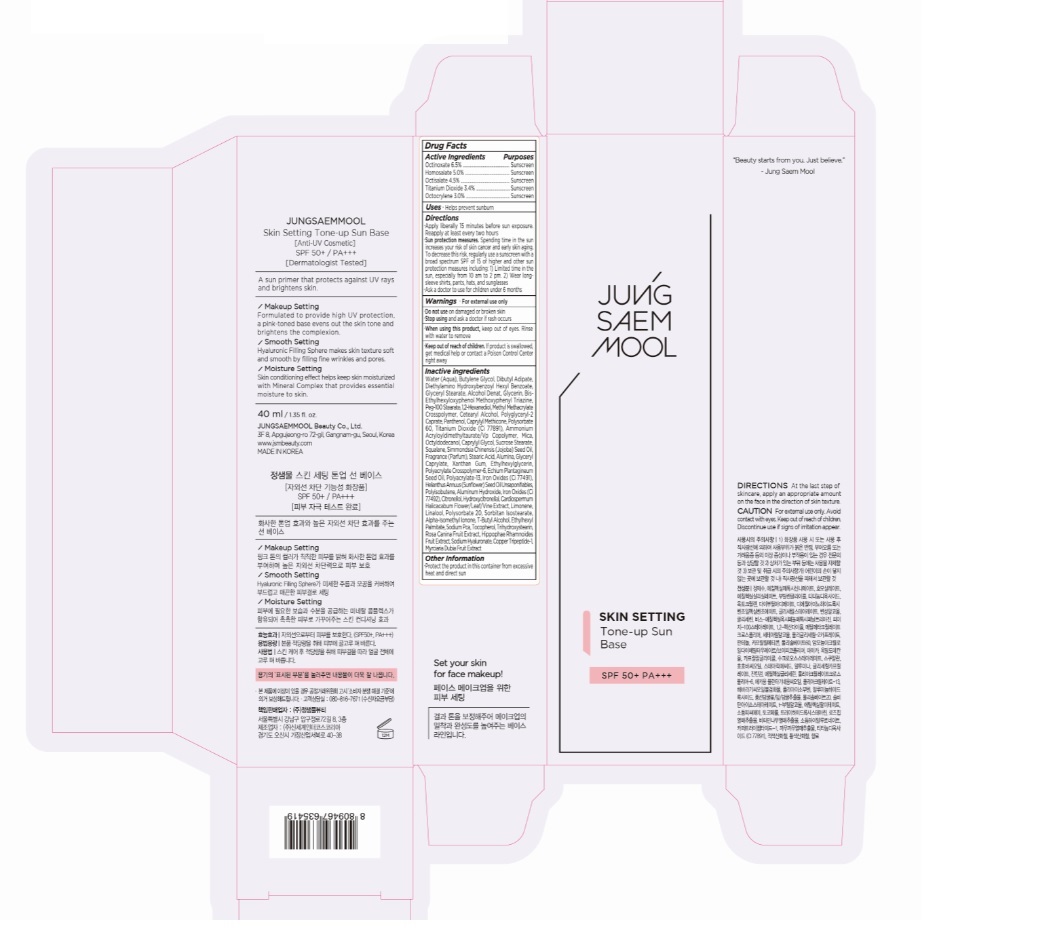 DRUG LABEL: JUNGSAEMMOOL SKIN SETTING TONE-UP SUN BASE
NDC: 71261-018 | Form: CREAM
Manufacturer: Jungsaemmool Beauty Co., Ltd.
Category: otc | Type: HUMAN OTC DRUG LABEL
Date: 20210218

ACTIVE INGREDIENTS: TITANIUM DIOXIDE 34 mg/1 mL; HOMOSALATE 50 mg/1 mL; OCTINOXATE 65 mg/1 mL; OCTISALATE 45 mg/1 mL; OCTOCRYLENE 30 mg/1 mL
INACTIVE INGREDIENTS: WATER; BUTYLENE GLYCOL; DIBUTYL ADIPATE; DIETHYLAMINO HYDROXYBENZOYL HEXYL BENZOATE; GLYCERYL MONOSTEARATE; ALCOHOL; GLYCERIN; BEMOTRIZINOL; PEG-100 STEARATE; 1,2-HEXANEDIOL; METHYL METHACRYLATE/GLYCOL DIMETHACRYLATE CROSSPOLYMER; CETOSTEARYL ALCOHOL; POLYGLYCERYL-2 CAPRATE; PANTHENOL; CAPRYLYL TRISILOXANE; POLYSORBATE 60; AMMONIUM ACRYLOYLDIMETHYLTAURATE/VP COPOLYMER; MICA; OCTYLDODECANOL; CAPRYLYL GLYCOL; SUCROSE STEARATE; SQUALANE; JOJOBA OIL; STEARIC ACID; ALUMINUM OXIDE; GLYCERYL MONOCAPRYLATE; XANTHAN GUM; ETHYLHEXYLGLYCERIN; AMMONIUM ACRYLOYLDIMETHYLTAURATE, DIMETHYLACRYLAMIDE, LAURYL METHACRYLATE AND LAURETH-4 METHACRYLATE COPOLYMER, TRIMETHYLOLPROPANE TRIACRYLATE CROSSLINKED (45000 MPA.S); ECHIUM PLANTAGINEUM SEED OIL; FERRIC OXIDE RED; POLYISOBUTYLENE (1000 MW); ALUMINUM HYDROXIDE; FERRIC OXIDE YELLOW; .BETA.-CITRONELLOL, (R)-; HYDROXYCITRONELLAL; CARDIOSPERMUM HALICACABUM FLOWERING TOP; LIMONENE, (+)-; LINALOOL, (+/-)-; POLYSORBATE 20; SORBITAN ISOSTEARATE; ISOMETHYL-.ALPHA.-IONONE; TERT-BUTYL ALCOHOL; ETHYLHEXYL PALMITATE; SODIUM PYRROLIDONE CARBOXYLATE; TOCOPHEROL; TRIHYDROXYSTEARIN; ROSA CANINA FRUIT; HIPPOPHAE RHAMNOIDES FRUIT; HYALURONATE SODIUM; PREZATIDE COPPER; MYRCIARIA DUBIA FRUIT

71261-018_JUNGSAEMMOOL SKIN SETTING TONE-UP SUN BASE

ACTIVE INGREDIENT

Octinoxate 6.5%

Homosalate 5.0%

Octisalate 4.5%

Titanium Dioxide 3.4%

Octocrylene 3.0%

PURPOSE

Sunscreen

INDICATIONS AND USAGE

Helps prevent sunburn

DOSAGE AND ADMINISTRATION

Apply liberally 15 minutes before sun exposure. Reapply at least every two hours

Sun protection measures. Spending time in the sun increases your risk of skin cancer and early skin aging. To decrease this risk, regularly use a sunscreen with a broad spectrum SPF of 15 of higher and other sun protection measures including: 1) Limited time in the sun, especially from 10 am to 2 pm. 2) Wear long-sleeve shirts, pants, hats, and sunglasses

Ask a doctor to use for children under 6 months

WARNINGS

For external use only

Do not use on damaged or broken skin

When using this product, keep out of eyes. Rinse with water to remove.

Stop using and ask a doctor if rash occurs.

KEEP OUT OF REACH OF CHILDREN

Keep out of reach of the children. If product is swallowed, get medical help or contact a poison control center right away.

INACTIVE INGREDIENT

WATER (AQUA), BUTYLENE GLYCOL, DIBUTYL ADIPATE, DIETHYLAMINO HYDROXYBENZOYL HEXYL BENZOATE, GLYCERYL STEARATE, ALCOHOL DENAT., GLYCERIN, BIS-ETHYLHEXYLOXYPHENOL METHOXYPHENYL TRIAZINE, PEG-100 STEARATE, 1,2-HEXANEDIOL, METHYL METHACRYLATE CROSSPOLYMER, CETEARYL ALCOHOL, POLYGLYCERYL-2 CAPRATE, PANTHENOL, CAPRYLYL METHICONE, POLYSORBATE 60, TITANIUM DIOXIDE (CI 77891), AMMONIUM ACRYLOYLDIMETHYLTAURATE/VP COPOLYMER, MICA, OCTYLDODECANOL, CAPRYLYL GLYCOL, SUCROSE STEARATE, SQUALANE, SIMMONDSIA CHINENSIS (JOJOBA) SEED OIL, FRAGRANCE (PARFUM), STEARIC ACID, ALUMINA, GLYCERYL CAPRYLATE, XANTHAN GUM, ETHYLHEXYLGLYCERIN, POLYACRYLATE CROSSPOLYMER-6, ECHIUM PLANTAGINEUM SEED OIL, POLYACRYLATE-13, IRON OXIDES (CI 77491), HELIANTHUS ANNUUS (SUNFLOWER) SEED OIL UNSAPONIFIABLES, POLYISOBUTENE, ALUMINUM HYDROXIDE, IRON OXIDES (CI 77492), CITRONELLOL, HYDROXYCITRONELLAL, CARDIOSPERMUM HALICACABUM FLOWER/LEAF/VINE EXTRACT, LIMONENE, LINALOOL, POLYSORBATE 20, SORBITAN ISOSTEARATE, ALPHA-ISOMETHYL IONONE, t-BUTYL ALCOHOL, ETHYLHEXYL PALMITATE, SODIUM PCA, TOCOPHEROL, TRIHYDROXYSTEARIN, ROSA CANINA FRUIT EXTRACT, HIPPOPHAE RHAMNOIDES FRUIT EXTRACT, SODIUM HYALURONATE, COPPER TRIPEPTIDE-1, MYRCIARIA DUBIA FRUIT EXTRACT

OTHER SAFETY INFORMATION

Protect the product in the container from excessive heat and direct sun